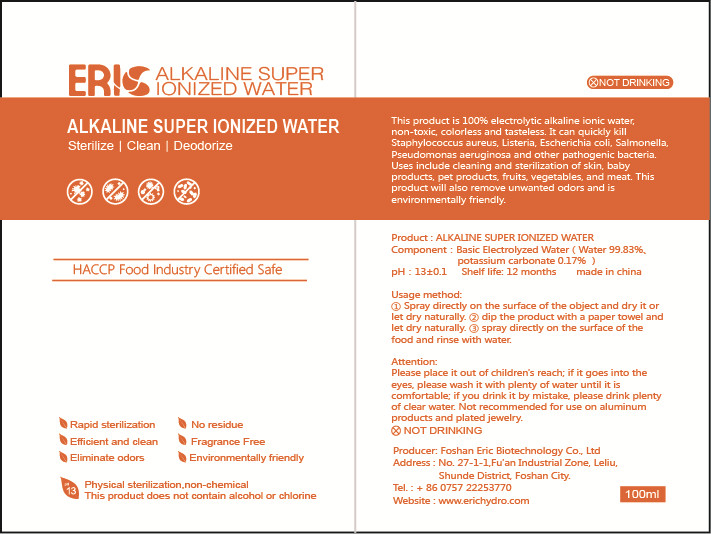 DRUG LABEL: Alkaline Super Ionized Water
NDC: 41768-001 | Form: SPRAY
Manufacturer: Foshan Eric Biotechnology Co., Ltd.
Category: homeopathic | Type: HUMAN OTC DRUG LABEL
Date: 20200608

ACTIVE INGREDIENTS: POTASSIUM CARBONATE 0.17 g/100 mL
INACTIVE INGREDIENTS: WATER

DOSAGE AND ADMINISTRATION

Store in a cool and dry place

INACTIVE INGREDIENT

Pure Water

INDICATIONS AND USAGE

①Spray directly on the surface of the object and dry it or let dry naturally.

②dip the product with a paper towel and let dry naturally.

③spray directly on the surface of the food and rinse with water.

ACTIVE INGREDIENT

potassium carbonate

keep out of reach of children

PURPOSE

Disinfection
Sterilization

WARNINGS

Please place it out of children's reach; if it goes into the eyes, please wash it with plenty of water until it is comfortable; if you drink it by mistake, please drink plenty of clear water. Not recommended for use on aluminum products and plated jewelry.